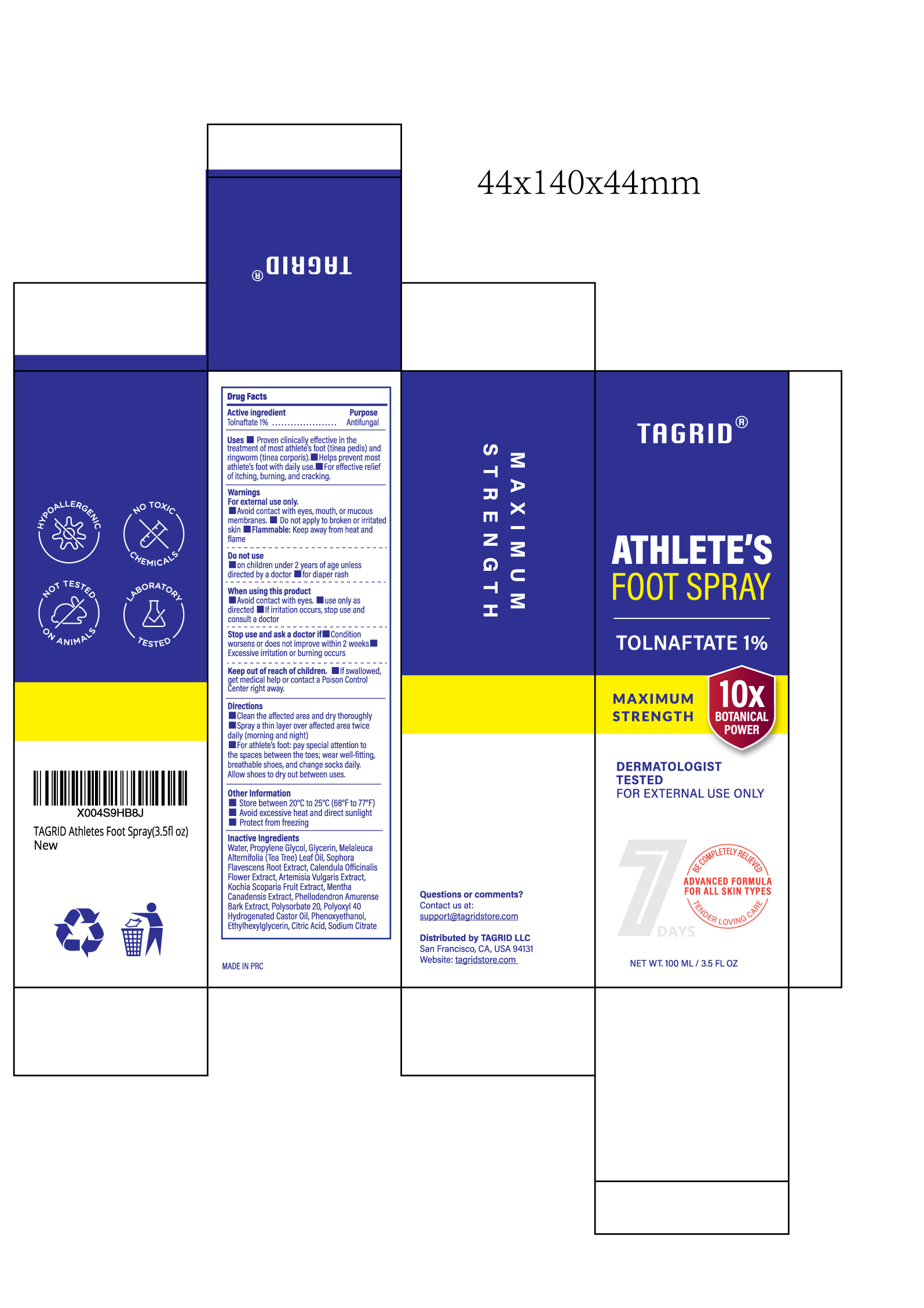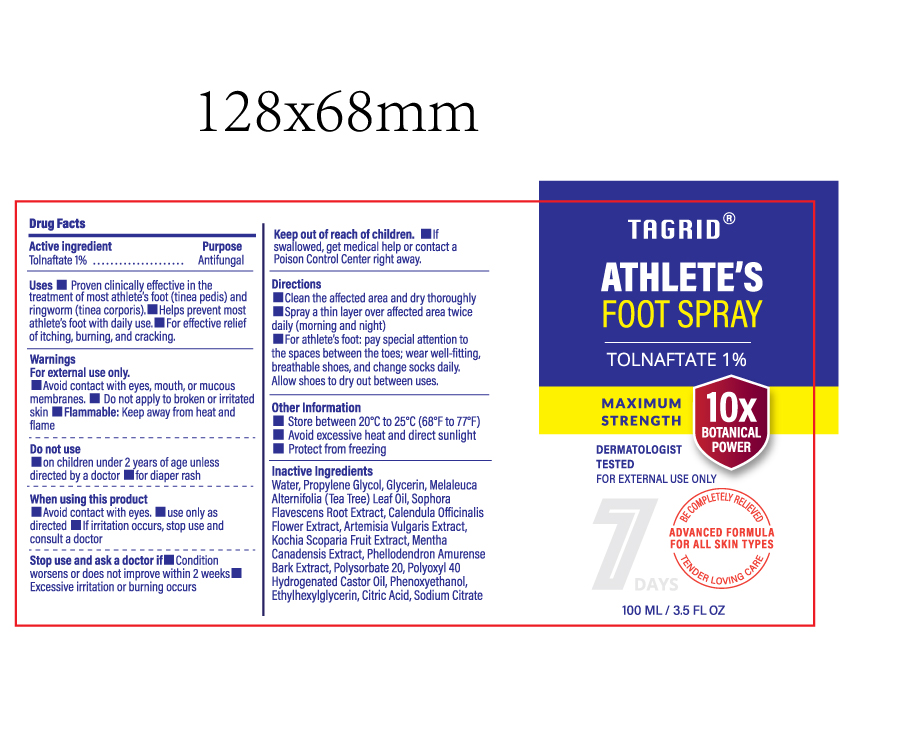 DRUG LABEL: Tagrid Athlete Foot Antifungal with Tolnaftate
NDC: 85384-0017 | Form: SPRAY
Manufacturer: TAGRID LLC
Category: otc | Type: HUMAN OTC DRUG LABEL
Date: 20250810

ACTIVE INGREDIENTS: Tolnaftate 1 g/100 mL
INACTIVE INGREDIENTS: WATER; PROPYLENE GLYCOL; GLYCERIN; TEA TREE OIL; SOPHORA FLAVESCENS ROOT; CALENDULA OFFICINALIS FLOWER; ARTEMISIA VULGARIS ROOT; BASSIA SCOPARIA FRUIT; MENTHA CANADENSIS TOP; PHELLODENDRON AMURENSE BARK; POLYSORBATE 20; POLYOXYL 40 HYDROGENATED CASTOR OIL; PHENOXYETHANOL; ETHYLHEXYLGLYCERIN; CITRIC ACID MONOHYDRATE; DISODIUM HYDROGEN CITRATE

Initial Drug Listing - Initial Drug Listing - Tagrid Athlete's Foot Spray Tolnaftate 1%

Active ingredient:

1. Tolnaftate 1%

PURPOSE

1. Antifungal

Uses:

1. Proven clinically effective in the treatment of most athlete’s foot (tinea pedis) and ringworm (tinea corporis).
2. Helps prevent most athlete’s foot with daily use.
3. For effective relief of itching, burning, and cracking.

WARNINGS

- For external use only.
- Avoid contact with eyes, mouth, or mucous membranes.
- Do not apply to broken or irritated skin.
- Flammable: Keep away from heat and flame.

Do not use:

- On children under 2 years of age unless directed by a doctor.
- For diaper rash.

When using this product

- Avoid contact with eyes.
- Use only as directed.
- If irritation occurs, stop use and consult a doctor.

Stop use and ask a doctor if

- Condition worsens or does not improve within 2 weeks.
- Excessive irritation or burning occurs.

Keep out of reach of children.

If swallowed, get medical help or contact a Poison Control Center right away.

Directions:

- Clean the affected area and dry thoroughly.
- Spray a thin layer over affected area twice daily (morning and night).
- For athlete’s foot: pay special attention to the spaces between the toes; wear well-fitting, breathable shoes, and change socks daily. Allow shoes to dry out between uses.

Inactive ingredients:

- Water
- Artemisia vulgaris extract
- Kochia scoparia fruit extract
- Dictamnus dasycarpus root extract
- Smilax glabra root extract
- Solidago decurrens fruiting top extract
- Phellodendron amurense bark extract
- Euphorbia fischeriana root extract
- Gleditsia sinensis fruit extract
- Stemona tuberosa root extract

OTHER SAFETY INFORMATION

- Store between 20°C to 25°C (68°F to 77°F).
- Avoid excessive heat and direct sunlight.
- Protect from freezing.

Questions or comments?

Contact us at support@tagridstore.com

PACKAGE LABEL.PRINCIPAL DISPLAY PANEL

Available in 100 mL, 50 mL and 30 mL can. All packages look the same externally, with the only variation being fill volume.